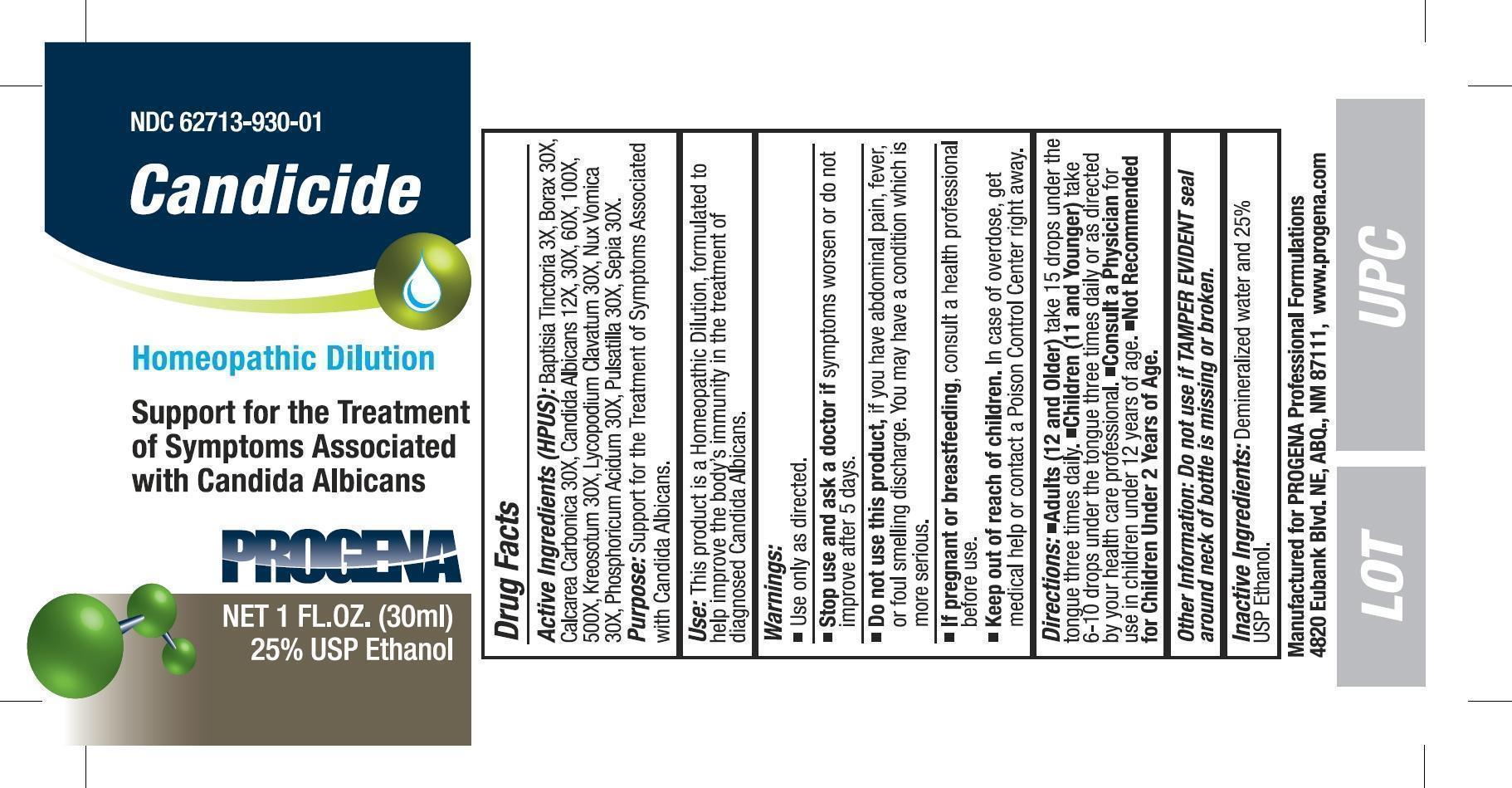 DRUG LABEL: Candicide
NDC: 62713-930 | Form: LIQUID
Manufacturer: Meditrend, Inc. DBA Progena Professional Formulations
Category: homeopathic | Type: HUMAN OTC DRUG LABEL
Date: 20151125

ACTIVE INGREDIENTS: BAPTISIA TINCTORIA ROOT 3 [hp_X]/1 mL; SODIUM BORATE 30 [hp_X]/1 mL; OYSTER SHELL CALCIUM CARBONATE, CRUDE 30 [hp_X]/1 mL; CANDIDA ALBICANS 500 [hp_X]/1 mL; WOOD CREOSOTE 30 [hp_X]/1 mL; LYCOPODIUM CLAVATUM SPORE 30 [hp_X]/1 mL; STRYCHNOS NUX-VOMICA SEED 30 [hp_X]/1 mL; PHOSPHORIC ACID 30 [hp_X]/1 mL; PULSATILLA VULGARIS 30 [hp_X]/1 mL; SEPIA OFFICINALIS JUICE 30 [hp_X]/1 mL
INACTIVE INGREDIENTS: ALCOHOL; WATER

Candicide

Active Ingredients (HPUS): Baptisia Tinctoria 3X, Borax 30X,
Calcarea Carbonica 30X, Candida Albicans (12X, 30x, 60x, 100x, 500x), Kreosotum 30X,
Lycopodium Clavatum 30X, Nux Vomica 30X, Phosphoricum
Acidum 30X, Pulsatilla 30X, Sepia 30X.

PURPOSE

Purpose: Support for the Treatment of Symptoms Associated with
Candida Albicans.

INDICATIONS AND USAGE

Use: This product is a Homeopathic Dilution, formulated to help
improve the body’s immunity in the treatment of diagnosed
Candida Albicans.

Warnings:
Use only as directed.

Stop use and ask a doctor if symptoms worsen or do not
improve after 5 days.

Do not use this product, if you have abdominal pain, fever, or foul
smelling discharge. You may have a condition which is more serious.

PREGNANCY OR BREAST FEEDING

If pregnant or breast-feeding, consult a health professional
before use.

Keep out of reach of children. In case of overdose, get medical
help or contact a Poison Control Center right away.

DOSAGE AND ADMINISTRATION

Directions: Adults (12 and Older) take 15 drops under the
tongue three times daily. Children (11 and Younger) take 10 drops
under the tongue three times daily or as directed by your health
care professional. Consult a Physician for use in children under
12 years of age. Not Recommended for Children Under 2
Years of Age.

Other Information: Do not use if TAMPER EVIDENT seal
around neck of bottle is missing or broken.

Inactive Ingredients: Demineralized water and 25% USP Ethanol.

PACKAGE LABEL

Manufactured for PROGENA Professional Formulations
4820 Eubank Blvd. NE, ABQ., NM 87111, www.progena.com